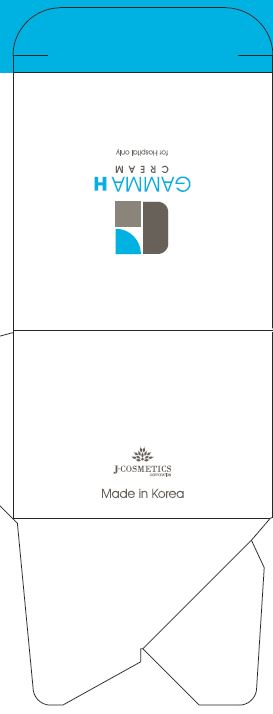 DRUG LABEL: Gamma HCream
NDC: 70488-0009 | Form: CREAM
Manufacturer: MUSEE Cosmetic Co.,Ltd.
Category: otc | Type: HUMAN OTC DRUG LABEL
Date: 20190104

ACTIVE INGREDIENTS: GLYCERIN 8 g/100 mL
INACTIVE INGREDIENTS: WATER; SHEA BUTTER

Drug Facts

ACTIVE INGREDIENT

glycerin

INACTIVE INGREDIENT

Water, Bentonite, SparassisCrispa Extract, Mineral oil, Cetearyl Alcohol, ButyrospermumParkii (Shea) Butter, Theobroma Cacao (Cocoa) Seed Butter, Hydrogenated Polyisobutene, CetylEthylhexanoate, Stearyl alcohol, Beeswax, Cocos Nucifera (Coconut) Oil, Cyclopentasiloxane, 1,2-Hexanediol, Olea Europaea (Olive) Fruit Oil, Cyclohexasiloxane, Cetearyl Glucoside, Dimethicone/Vinyl DimethiconeCrosspolymer, Dimethicone, Glyceryl Stearate, Disodium EDTA

PURPOSE

for skin protectant

keep out of reach of the children

INDICATIONS AND USAGE

Apply to the skin and gently rub it to absorb it

WARNINGS

1. Do not use in the following cases(Eczema and scalp wounds)
2.Side Effects
1)Due to the use of this druf if rash, irritation, itching and symptopms of hypersnesitivity occur dicontinue use and consult your phamacisr or doctor
3.General Precautions
1)If in contact with the eyes, wash out thoroughty with water If the symptoms are servere, seek medical advice immediately
2)This product is for exeternal use only. Do not use for internal use
4.Storage and handling precautions
1)If possible, avoid direct sunlight and store in cool and area of low humidity
2)In order to maintain the quality of the product and avoid misuse
3)Avoid placing the product near fire and store out in reach of children

DOSAGE AND ADMINISTRATION

for topical use only